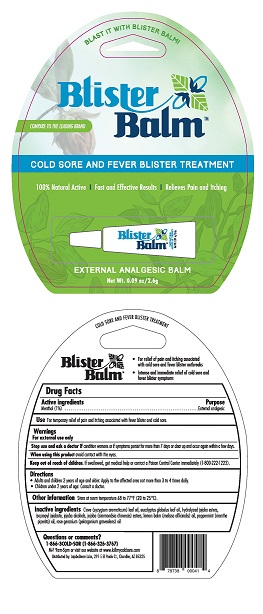 DRUG LABEL: Blister Balm
NDC: 70996-003 | Form: SALVE
Manufacturer: Floratech Botanicals, LLC
Category: otc | Type: HUMAN OTC DRUG LABEL
Date: 20181106

ACTIVE INGREDIENTS: MENTHOL 1 g/100 g
INACTIVE INGREDIENTS: EUCALYPTUS GLOBULUS LEAF; HYDROLYZED JOJOBA ESTERS (ACID FORM); LEMON BALM OIL; ALPROSTADIL ISOPROPYL ESTER; CLOVE LEAF OIL; PELARGONIUM ROSEUM OIL; PEPPERMINT OIL; HYDROGENATED JOJOBA OIL

PURPOSE

External analgesic

Active Ingredients

Menthol 1%

Purpose

External Analgesic - cold sore or fever blister treatment

Uses:

For relief of pain and itching associated with cold sore and fever blister outbreaks.

Intense and immediate blocking of cold sore and gever blister symptoms.

Warnings

For external use only.

Keep out of reach of children.

If swallowed, get medical help or contact a Poison Control Center right away.

keep out of reach of children. If swallowed get medical help or contact a poison control center immediately. (1-800-222-1222)

Stop use and ask doctor if condition worsen or if symptoms persist for more than 7 days or clear up and occur again within a few days.

When using this product avoid contact with the eyes

keep out of Reach of children. If swallowed, get medical help or contact a poison control center immediately. (1-800-222-1222)

Directions

- Adults and children 2 years of age and older. Apply to the afftected area not more than 3 to 4 times daily.
- Children under 2 years of age: consult a doctor

Inactive Ingredients

camphor

clove (syzygium aromaticum) leaf oil

eucalyptus globulus leaf oil

hydrolyzed jojoba esters

isopropyl jojobate

jojoba (simmondsia chinensis) esters

jojoba alcohols

lemon balm (melissa officinalis) oil

peppermint (menthe piperita) oil

rose geranium (pelargonium graveolens) oil